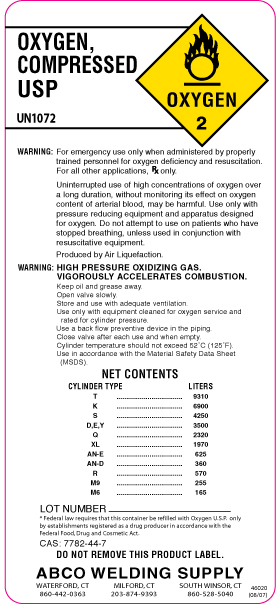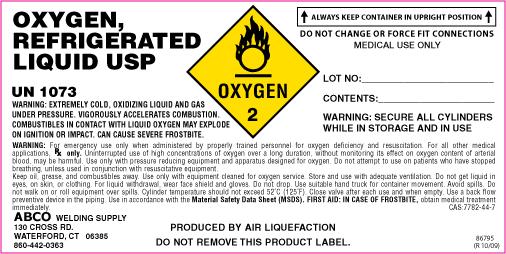 DRUG LABEL: Oxygen
NDC: 54949-001 | Form: GAS
Manufacturer: ABCO Welding and Industrial Supply Inc
Category: prescription | Type: HUMAN PRESCRIPTION DRUG LABEL
Date: 20100730

ACTIVE INGREDIENTS: Oxygen 995 mL/1 L

oxygen

PACKAGE LABEL

OXYGEN, COMPRESSED USPUN1073

WARNING: For emergency use only when administered by properly trained personnel for oxygen deficiency and resuscitation. For all other applications, Rx only. Uninterrupted use of high concentrations of oxygen over a long duration, without monitoring its effect on oxygen content of arterial blood, may be harmful. Use only with pressure reducing equipment and apparatus designed for oxygen. Do not attempt to use on patients who have stopped breathing, unless used in conjunction with resuscitative equipment.

Produced by Air Liquefaction.

WARNING: HIGH PRESSURE OXIDIZING GAS, VIGOROUSLY ACCELERATES COMBUSTION.

Keep oil, grease, and combustibles away. Open valve slowly. Store and use with adequate ventilation. Use only with equipment cleaned for oxygen service. Store and use with adequate ventilation. Use only with equipment cleaned for oxygen service and rated for cylinder pressure. Use a back flow preventive device in the piping. Close valve after each use and when empty. Cylinder temperature should not exceed 52˚C (125˚F).

NET CONTENTS

CYLINDER TYPE LITERS

T-9310

k-6900

S-4250

D,E,Y-3500

Q-2320

XL-1970

AN-E-625

AN-D-360

R-570

M9-255

M6-165

LOT NUMBER

*federal Law requires that this container be refilled with Oxygen USP only be establishments registered as a drug produce in accordance with the Federal Food Drug and Cosmetic Act

CAS: 7782-44-7

DO NOT REMOVE THIS PRODUCT LABEL.

ABCO WELDING SUPPLY 130 CROSS RD. WATERFORD, CT 06385 860-442-0363

MILFORD, CT 203-874-9191

SOUTH WINSOR, CT 860-528-5040

PACKAGE LABEL

OXYGEN, REFRIGERATED LIQUID USP UN1073
WARNING: EXTREMELY COLD, OXIDIZING LIQUID AND GAS UNDER PRESSURE. VIGOROUSLY ACCELERATES COMBUSTION. COMBUSTIBLES IN CONTACT WITH LIQUID OXYGEN MAY EXPLODE ON IGNITION OR IMPACT. CAN CAUSE SEVERE FROSTBITE.
WARNING: For emergency use only when administered by properly trained personnel for oxygen deficiency and resuscitation. For all other medical applications, Rx only. Uninterrupted use of high concentrations of oxygen over a long duration, without monitoring its effect on oxygen content of arterial blood, may be harmful. Use only with pressure reducing equipment and apparatus designed for oxygen. Do not attempt to use on patients who have stopped breathing, unless used in conjunction with resuscitative equipment.
Keep oil, grease, and combustibles away. Use only with equipment cleaned for oxygen service. Store and use with adequate ventilation. Do not get liquid in eyes, on skin, or clothing. For liquid withdrawal, wear face shield and gloves. Do not drop. Use suitable hand truck for container movement. Avoid spills. Do not walk on or roll equipment over spills. Cylinder temperature should not exceed 52˚C (125˚F). Close valve after each use and when empty. Use a back flow preventive device in the piping. Use in accordance with the Material Safety Data Sheet (MSDS).
CAS: 7782-44-7
86795 (R 10/09)
ABCO WELDING SUPPLY 130 CROSS RD. WATERFORD, CT 06385 860-442-0363
PRODUCED BY AIR LIQUEFACTION DO NOT REMOVE THIS PRODUCT LABEL
ALWAYS KEEP CONTAINER IN UPRIGHT POSITION
DO NOT CHANGE OR FORCE FIT CONNECTIONS MEDICAL USE ONLY
LOT NO:
CONTENTS:
WARNING: SECURE ALL CYLINDERS WHILE IN STORAGE AND USE